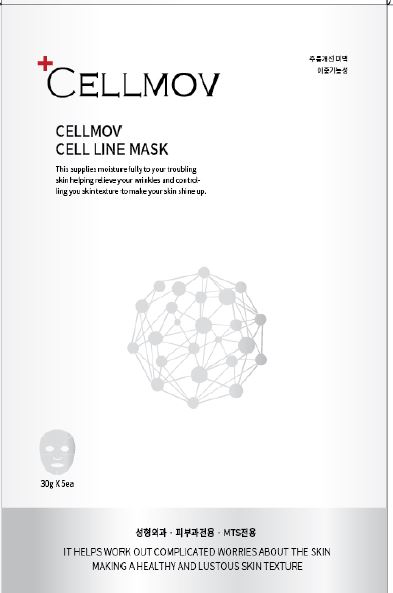 DRUG LABEL: CELLMOV CELL LINE MASK
NDC: 72818-0001 | Form: LIQUID
Manufacturer: Cellmov Co., Ltd.
Category: otc | Type: HUMAN OTC DRUG LABEL
Date: 20190129

ACTIVE INGREDIENTS: NIACINAMIDE 2 g/100 g; ADENOSINE 0.04 g/100 g; GLYCERIN 8 g/100 g
INACTIVE INGREDIENTS: WATER

Drug Facts

ACTIVE INGREDIENT

niacinamide, adenosine, glycerin

INACTIVE INGREDIENT

water, butylene glycol,carbomer, triethanolamine, alcohol, allantoin, etc.

PURPOSE

Anti Wrinkle, whitening

keep out of reach of the children

INDICATIONS AND USAGE

1. Thoroughly wash and gently wipe out your face with toner.

2. Take out and unfold the mask and apply on your face.

3. Remove the mask after 10~20 minutes and let the skin absorb the remaining essence by gently patting the skin

WARNINGS

1. If abnormal symptoms or side effects such as red spots, swelling, or itching are present in the cosmetics or in the direct sunlight after use, consult a specialist

2. Do not use in wounded areas

3. Precautions for storage and handling

- Keep out of reach of children

- Keep away from direct sunlight

4. Avoid the use of eye area

DOSAGE AND ADMINISTRATION

for external use only